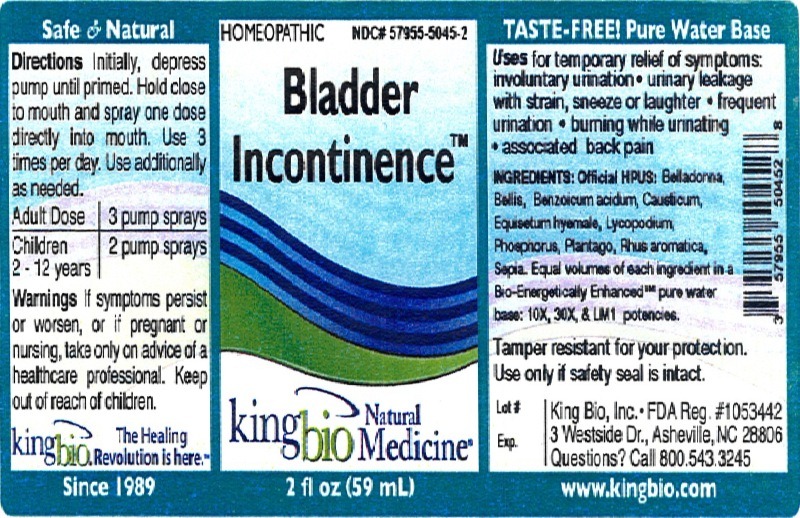 DRUG LABEL: Bladder Incontinence
NDC: 57955-5045 | Form: LIQUID
Manufacturer: King Bio Inc.
Category: homeopathic | Type: HUMAN OTC DRUG LABEL
Date: 20120619

ACTIVE INGREDIENTS: ATROPA BELLADONNA 10 [hp_X]/59 mL; BELLIS PERENNIS 10 [hp_X]/59 mL; BENZOIC ACID 10 [hp_X]/59 mL; CAUSTICUM 10 [hp_X]/59 mL; EQUISETUM HYEMALE 10 [hp_X]/59 mL; LYCOPODIUM CLAVATUM SPORE 10 [hp_X]/59 mL; PHOSPHORUS 10 [hp_X]/59 mL; PLANTAGO MAJOR 10 [hp_X]/59 mL; RHUS AROMATICA ROOT BARK 10 [hp_X]/59 mL; SEPIA OFFICINALIS JUICE 10 [hp_X]/59 mL
INACTIVE INGREDIENTS: WATER

Bladder Incontinence

Active Ingredients

Official HPUS: Belladonna, Bellis perennis, Benzoicum acidum, Causticum, Equisetum hyemale, Lycopodium clavatum, Phosphorus, Plantago major, Rhus aromatica, Sepia.

Reference image bladderincontinence.jpg

Inactive Ingredient

Equal volumes of each ingredient in a Bio-Energetically Enhanced pure water base: 10X, 30X, and LM1 potencies.

Reference image bladderincontinence.jpg

Purpose

Uses for temporary relief of symptoms:

- involuntary urination
- urinary leakage with strain, sneeze or laughter
- frequent urination
- burning while urinating
- associated back pain

Reference image bladderincontinence.jpg

Dosage and Administration

Directions: Initially, depress pump until primed. Hold close to mouth and spray one dose directly into mouth. Use 3 times per day. Use additionally as needed.

Adult Dose 3 pump sprays

Children 2 - 12 years 2 pump sprays

Reference image badderincontinence.jpg

Warnings

If symptoms persist or worsen, or if pregnant or nursing, take only on advice of a healthcare professional. Keep out of reach of children.

Other: Tamper resistant for your protection. Use only if safety seal is intact.

Reference image bladderincontinence.jpg

Keep out of reach of children.

Reference image bladderincontinence.jpg

Indications and Usage

Uses for temporary relief of symptoms: involuntary urination, urinary leakage with strain, sneeze or laughter, frequent urination, burning while urinating and associated back pain.

Reference image bladderincontinence.jpg

PACKAGE LABEL

King Bio Inc.

3 Westside Drive

Asheville, NC 28806

Questions? Call 800.543.3245

www.kingbio.com